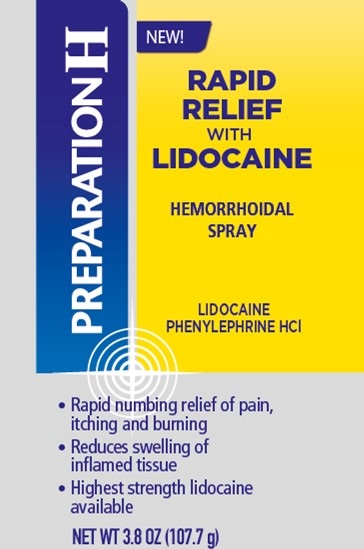 DRUG LABEL: Preparation H Rapid Relief
NDC: 0573-2890 | Form: SPRAY
Manufacturer: Haleon US Holdings LLC
Category: otc | Type: HUMAN OTC DRUG LABEL
Date: 20240229

ACTIVE INGREDIENTS: LIDOCAINE 50 mg/1 g; PHENYLEPHRINE HYDROCHLORIDE 2.5 mg/1 g
INACTIVE INGREDIENTS: ALOE VERA LEAF; ANHYDROUS CITRIC ACID; EDETATE DISODIUM; GLYCERIN; ISOBUTANE; MALIC ACID; MENTHOL, UNSPECIFIED FORM; PROPYL GALLATE; PROPYLENE GLYCOL; ALCOHOL; SODIUM BENZOATE; WATER

Drug Facts

Active ingredients

Lidocaine 5%

Phenylephrine HCl 0.25%

Purposes

Local anesthetic

Vasoconstrictor

Uses

- Helps relieve the local discomfort and itching associated with hemorrhoids
- For the temporary relief of pain, soreness or burning
- Temporarily reduces the swelling associated with irritation in hemorrhoids
- Temporarily shrinks hemorrhoidal tissue

Warnings

For external use only

Flammable:Do not use while smoking or near heat or flame

Ask a doctor before use if you have

- heart disease
- high blood pressure
- thyroid disease
- diabetes
- difficulty in urination due to enlargement of the prostate gland

Ask a doctor or pharmacist before use if you arepresently taking a prescription drug for high blood pressure or depression.

When using this product

- do not exceed the recommended daily dosage unless directed by a doctor
- do not put this product into the rectum by using fingers or any mechanical device or applicator
- Warning -avoid spraying in eyes. Contents under pressure. Do not puncture or incinerate. Do not store at temperature above 120°F. Keep out of reach of children.
- Warning -use only as directed. Intentional misuse by deliberately concentrating and inhaling the contents can be harmful or fatal.

Stop use and ask a doctor if

- bleeding occurs
- condition worsens or does not improve within 7 days
- an allergic reaction develops
- the symptom being treated does not subside or if redness, irritation, swelling, pain, or other symptoms develop or increase

PREGNANCY OR BREAST FEEDING

If pregnant or breast-feeding,ask a health professional before use.

Keep out of reach of children.If swallowed, get medical help or contact a Poison Control Center right away.

Directions

- Adults: when practical, cleanse the affected area by patting or blotting with an appropriate cleansing pad
- Gently dry by patting or blotting with toilet tissue or a soft cloth before application of this product
- Shake well before using
- Hold 3 to 6” away from rectal area, spray to moisten and then wipe off excess, if desired
- Apply externally to the affected area up to 4 times daily
- Children under 12 years of age: consult a doctor

Other information

- Store at 20-25°C (68-77°F)

Inactive ingredients

aloe barbadensis leaf juice, citric acid, disodium EDTA, glycerin, isobutane, malic acid, menthol, propyl gallate, propylene glycol, SD alcohol 40-B, sodium benzoate, water

Questions or comments?

Call weekdays 9 AM to 5 PM EST at 1-800-99PrepHor 1-800-997-7374

Additional Information

No-Touch Spray

Do not use if clear safety seal around cap is broken or missing

Distributed by:

GSK Consumer Healthcare

Warren, NJ 07059

Trademarks are owned by or licensed to the GSK group of companies.

@2021 GSK or licensor

For most recent product information, visit www.preparationh.com

PRINCIPAL DISPLAY PANEL

NEW!

PREPARATIONH

RAPID RELIEF
WITH
LIDOCAINE

HEMORRHOIDAL SPRAY

LIDOCAINE
PHENYLEPHRINE HCl

- Rapid numbing relief of pain,
  itching and burning
- Reduces swelling of
  inflamed tissue
- Highest strength lidocaine
  available

NET WT 3.8 OZ (107.7 g)

000070918 Front Label